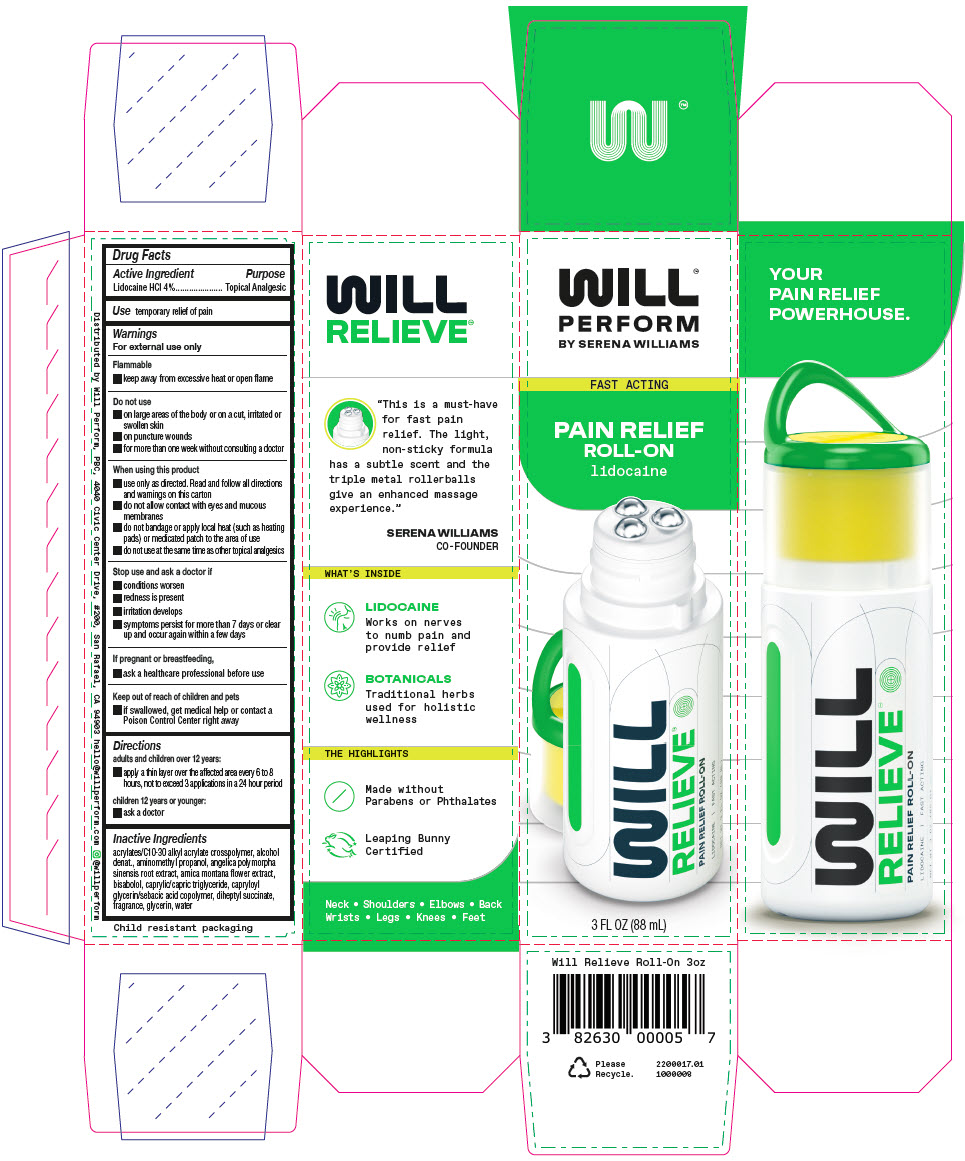 DRUG LABEL: Will Relieve Roll-On
NDC: 82630-002 | Form: GEL
Manufacturer: Will Perform, PBC
Category: otc | Type: HUMAN OTC DRUG LABEL
Date: 20230713

ACTIVE INGREDIENTS: Lidocaine Hydrochloride 3.2 g/88 mL
INACTIVE INGREDIENTS: Water; CARBOMER COPOLYMER TYPE B (ALLYL PENTAERYTHRITOL CROSSLINKED); Alcohol; Glycerin; Medium-Chain Triglycerides; DIHEPTYL SUCCINATE; CAPRYLOYL GLYCERIN/SEBACIC ACID COPOLYMER (2000 MPA.S); LEVOMENOL; ANGELICA SINENSIS ROOT; AMINOMETHYLPROPANOL; Arnica Montana Flower

Will Relieve™ Roll-On

Drug Facts

Active Ingredient

Lidocaine HCl 4%

Purpose

Topical Analgesic

Use

temporary relief of pain

Warnings

For external use only

Flammable

- keep away from excessive heat or open flame

Do not use

- on large areas of the body or on a cut, irritated or swollen skin
- on puncture wounds
- for more than one week without consulting a doctor

When using this product

- use only as directed. Read and follow all directions and warnings on this carton
- do not allow contact with eyes and mucous membranes
- do not bandage or apply local heat (such as heating pads) or medicated patch to the area of use
- do not use at the same time as other topical analgesics

Stop use and ask a doctor if

- conditions worsen
- redness is present
- irritation develops
- symptoms persist for more than 7 days or clear up and occur again within a few days

PREGNANCY OR BREAST FEEDING

If pregnant or breastfeeding,

- ask a healthcare professional before use

Keep out of reach of children and pets

- if swallowed, get medical help or contact a Poison Control Center right away

Directions

adults and children over 12 years:

- apply a thin layer over the affected area every 6 to 8 hours, not to exceed 3 applications in a 24 hour period

children 12 years or younger:

- ask a doctor

Inactive Ingredients

acrylates/C10-30 alkyl acrylate crosspolymer, alcohol denat., aminomethyl propanol, angelica polymorpha sinensis root extract, arnica montana flower extract, bisabolol, caprylic/capric triglyceride, capryloyl glycerin/sebacic acid copolymer, diheptyl succinate, fragrance, glycerin, water

Distributed by Will Perform, PBC, 4040 Civic Center Drive, #200, San Rafael, CA 94903

PRINCIPAL DISPLAY PANEL - 88 mL Bottle Carton

WILL™
PERFORM
BY SERENA WILLIAMS

FAST ACTING

PAIN RELIEF
ROLL-ON
lidocaine

3 FL OZ (88 mL)